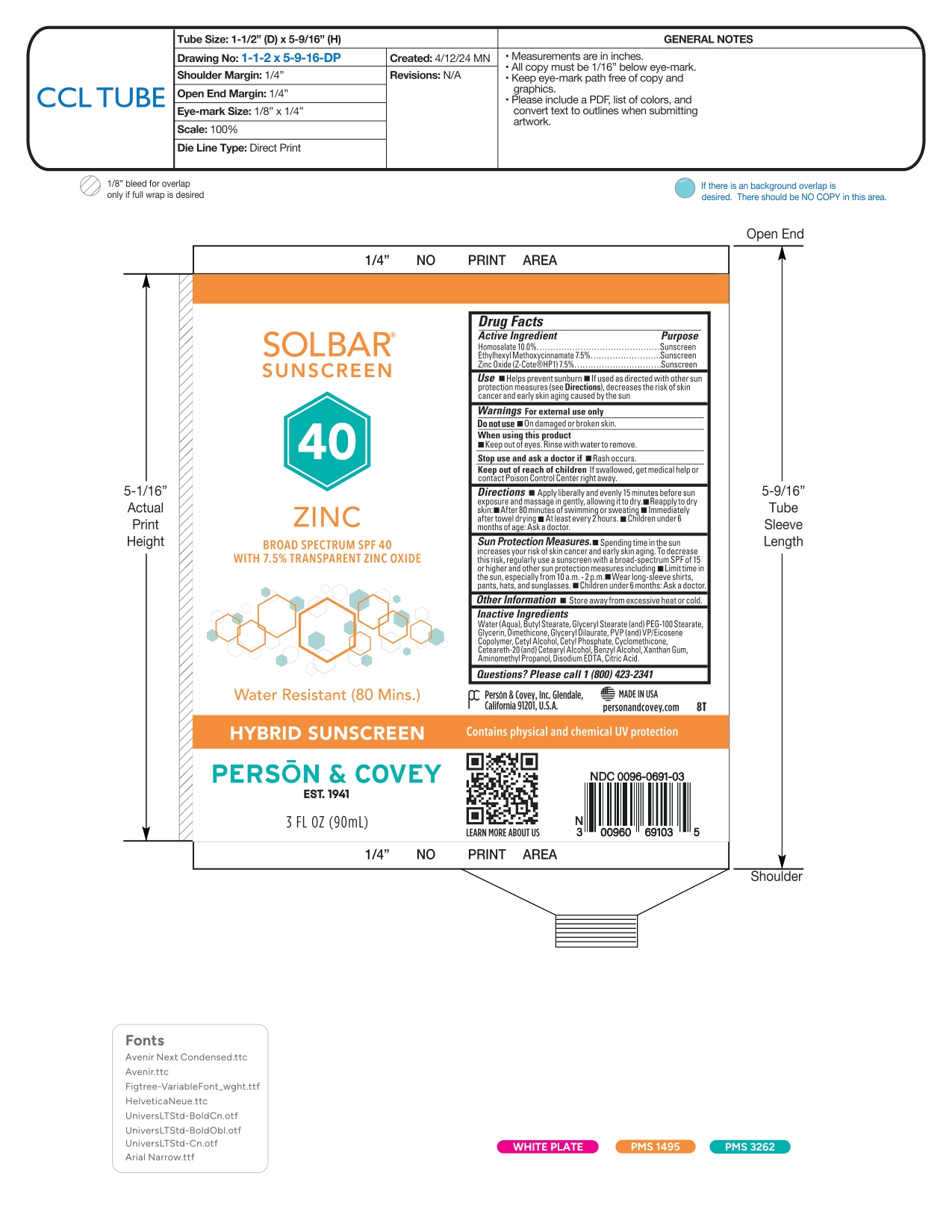 DRUG LABEL: SOLBAR SUNSCREEN 40 ZINC
NDC: 0096-0691 | Form: CREAM
Manufacturer: Person and Covey
Category: otc | Type: HUMAN OTC DRUG LABEL
Date: 20260122

ACTIVE INGREDIENTS: OCTINOXATE 75 mg/1 g; HOMOSALATE 100 mg/1 g; ZINC OXIDE 75 mg/1 g
INACTIVE INGREDIENTS: WATER; GLYCERYL MONOSTEARATE; BUTYL STEARATE; GLYCERYL DILAURATE; CETYL PHOSPHATE; CYCLOMETHICONE; AMINOMETHYL PROPANOL; POLYOXYL 20 CETOSTEARYL ETHER; CITRIC ACID; POVIDONE; CETYL ALCOHOL; XANTHAN GUM; EICOSYL POVIDONE; CETOSTEARYL ALCOHOL; DIMETHICONE; BENZYL ALCOHOL; GLYCERIN; PEG-100 STEARATE; EDETATE DISODIUM

SOLBAR ZINC - sunscreen cream

Active ingredient

Homosalate 10.0%

Ethylhexyl

Methoxycinnamate 7.5%

Zinc Oxide 7.5%

Purpose

Sunscreen

Use

- Helps prevent sunburn.
- If used as directed with other sun protection measures (see Directions), decreases the risk of skin cancer and early skin aging caused by the sun.

Warnings

For external use only

Do not use on damaged or broken skin.

When using this product keep out of eyes. Rinse with water to remove.

Stop use and ask a doctor if rash occurs.

Keep out of reach of children

If swallowed, get medical help or contact a Poison Control Center right away.

Directions

- Apply liberally and evenly 15 minutes before sun exposure.
- Reapply to dry skin:
- After 80 minutes of swimming or sweating
- Immediately after towel drying
- At least every 2 hours.
- Children under 6 months of age: Ask a doctor.

Sun Protection Measures.

- Spending time in the sun increases your risk of skin cancer and early skin aging. To decrease this risk, regularly use a sunscreen with a Broad Spectrum SPF value of 15 or higher and other sun protection measures including:
- Limit time in the sun, especially from 10 a.m. - 2 p.m.
- Wear long-sleeved shirts, pants, hats, and sunglasses.
- Children under 6 months: Ask a doctor.

Other Information

Store away from excessive heat or cold.

Inactive ingredient

Water (Aqua), Butyl Stearate, Glyceryl Stearate (and) PEG-100 Stearate, Glycerin, Dimethicone, Glyceryl Dilaurate, PVP (and) VP/Eicosene Copolymer, Cetyl Alcohol, Cetyl Phosphate, Cyclomethicone, Ceteareth-20 (and) Cetearyl Alcohol, Benzyl Alcohol, Xanthan Gum, Aminomethyl Propanol, Disodium EDTA, Citric Acid

Questions? Please call 1 (800) 423-2341

Company Information

Person & Covey, Inc. Glendale, California 91201, U.S.A. MADE IN USA personandcovey.com